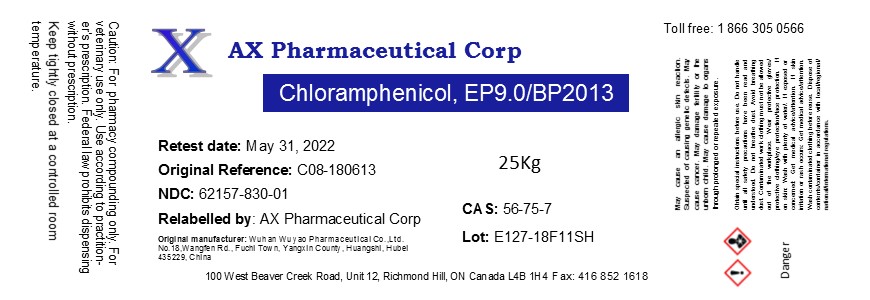 DRUG LABEL: Chloramphenicol
NDC: 62157-830 | Form: POWDER
Manufacturer: AX Pharmaceutical Corp
Category: other | Type: BULK INGREDIENT
Date: 20190429

ACTIVE INGREDIENTS: CHLORAMPHENICOL 1 kg/1 kg

Chloramphenicol